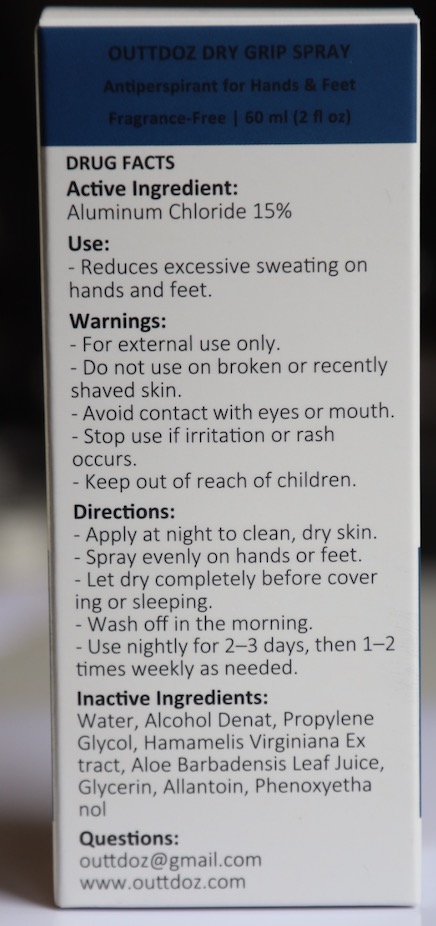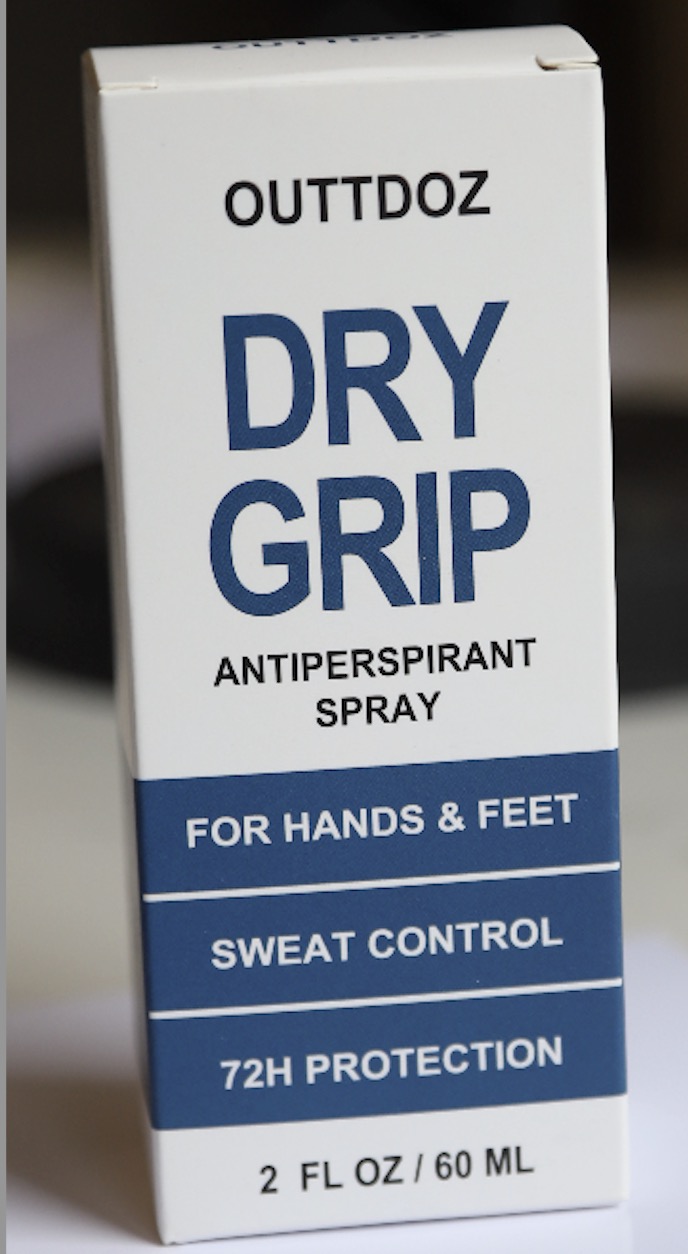 DRUG LABEL: DRY GRIP
NDC: 85751-001 | Form: SPRAY, METERED
Manufacturer: Chongqing Alefa Technology Co., Ltd.
Category: otc | Type: HUMAN OTC DRUG LABEL
Date: 20250603

ACTIVE INGREDIENTS: ALUMINUM CHLORIDE 15 g/100 g
INACTIVE INGREDIENTS: ALOE BARBADENSIS LEAF JUICE; PROPYLENE GLYCOL; ALCOHOL; HAMAMELIS VIRGINIANA LEAF; GLYCERIN; WATER; ALLANTOIN; PHENOXYETHANOL

INDICATIONS AND USAGE

Antiperspirant for Hands & Feet.
Apply at night to clean, dry skin.
Spray evenly on hands or feet.
Let dry completely before covering or sleeping.
Wash off in the morning.
Use nightly for 2–3 days, then 1–2 times weekly as needed.

WARNINGS

For external use only.
Do not use on broken or recently shaved skin.
Avoid contact with eyes or mouth.
Stop use if irritation or rash occurs.
Keep out of reach of children.

DOSAGE AND ADMINISTRATION

Apply to clean, dry hands and/or feet once daily.
Use preferably at bedtime.
Allow to dry completely before covering skin or putting on socks/shoes.

Keep out of reach of children.

PURPOSE

antiperspirant for hands & feet

ACTIVE INGREDIENT

Aluminum Chloride 15%(9g/60ml)

INACTIVE INGREDIENT

Water, Alcohol Denat, Propylene Glycol, Hamamelis Virginiana Extract, Aloe Barbadensis Leaf Juice, Glycerin, Allantoin, Phenoxyethanol